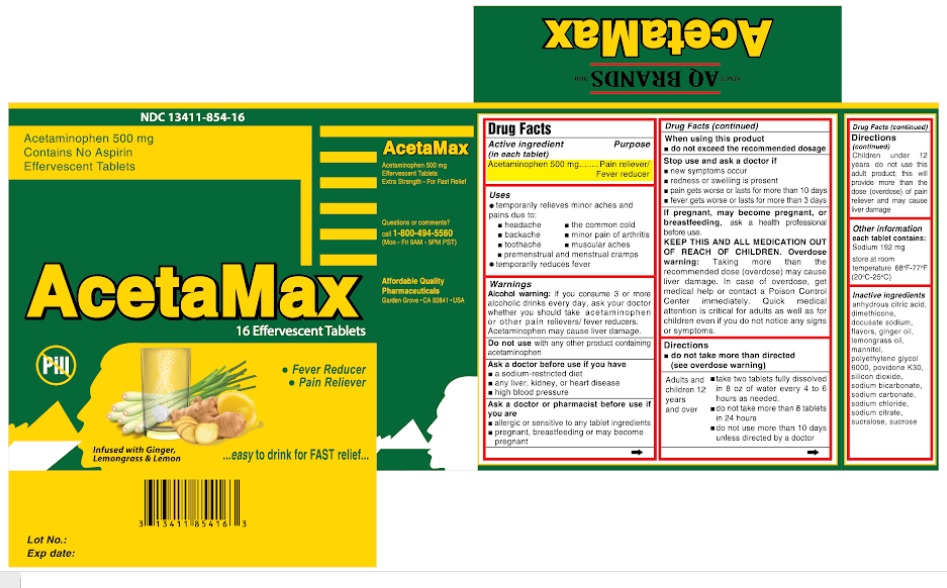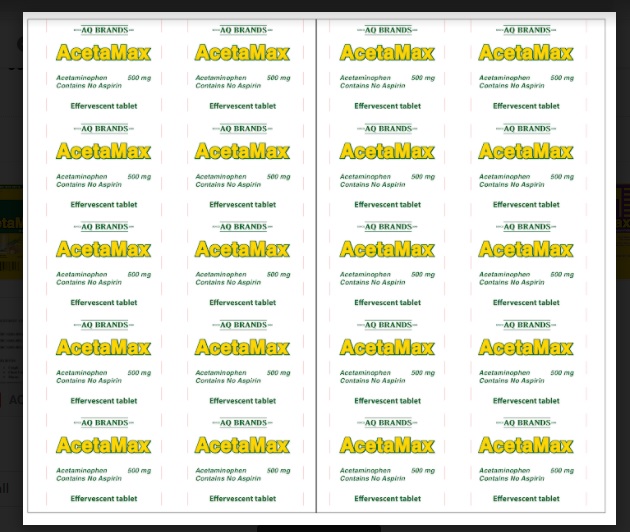 DRUG LABEL: AcetaMax
NDC: 13411-854 | Form: TABLET, EFFERVESCENT
Manufacturer: Advanced Pharmaceutical Services, Inc. Dba Affordable Quality Pharmaceuticals
Category: otc | Type: HUMAN OTC DRUG LABEL
Date: 20200831

ACTIVE INGREDIENTS: ACETAMINOPHEN 500 mg/1 1
INACTIVE INGREDIENTS: ANHYDROUS CITRIC ACID; DIMETHICONE; DOCUSATE SODIUM; GINGER OIL; WEST INDIAN LEMONGRASS OIL; MANNITOL; POLYETHYLENE GLYCOL 6000; POVIDONE K30; SILICON DIOXIDE; SODIUM BICARBONATE; SODIUM CARBONATE; SODIUM CHLORIDE; SODIUM CITRATE; SUCRALOSE; SUCROSE

AcetaMax

Active Ingredient

Acetaminophen 500 mg

Purpose

Pain reliever/ Fever Reducer

Uses

temporarily relieves minor aches and pains due to:
▪ headache
▪ backache
▪ toothache
▪ the common cold
▪ minor pain of arthritis
▪ muscular aches
▪ premenstrual and menstrual cramps
• temporarily reduces fever

Warnings

Alcohol warning: if you consume 3 or more alcoholic drinks every day, ask your doctor whether you should take acetaminophen or other pain relievers/ fever reducers.

Acetaminophen may cause liver damage.

Do not use with any other product containing acetaminophen

Ask a doctor before use if you have
• a sodium-restricted diet
• any liver, kidney, or heart disease
• high blood pressure

Ask a doctor or pharmacist before use if you are
• allergic or sensitive to any tablet ingredients
• pregnant, breastfeeding or may become pregnant
When using this product
• do not exceed the recommend dosage

Stop use and ask a doctor if
• new symptoms occur
• redness or swelling is present
• pain gets worse or lasts more than 10 days
• fever gets worse or lasts more than 3 days.

If pregnant, may become pregnant, or breastfeeding, ask a health professional before use.

KEEP THIS AND ALL MEDICATION OUT OF REACH OF CHILDREN.

Overdose warning: Taking more than the recommended dose (overdose) may cause liver damage. In case of overdose, get medical help or contact a Poison Control Center immediately. Quick medical attention is critical for adults as well as for children even if you do not notice any signs or symptoms.

Directions

• do not take more than directed (see overdose warning)

Adults and children 12 years and over
• take two tablets fully dissolved in 8 oz of water every 4 to 6 hours as needed.
• do not take more than 8 tablets in 24 hours.
• do not use more than 10 days unless directed by a doctor.
Children under 12 years do not use this adult product; this will provide more than the dose (overdose) of pain reliever and may cause liver damage.

Other information

Each tablet contains:
Sodium 192 mg.
Store at room temperature 68 F-77 F (20oC-25oC).

Inactive Ingredients

anhydrous citric acid, dimethicone, docusate sodium, flavors, ginger oil, lemongrass oil, mannitol, polyethylene glycol 6000, povidone K30, silicon dioxide, sodium bicarbonate, sodium carbonate, sodium chloride, sodium citrate, sucralose, sucrose.